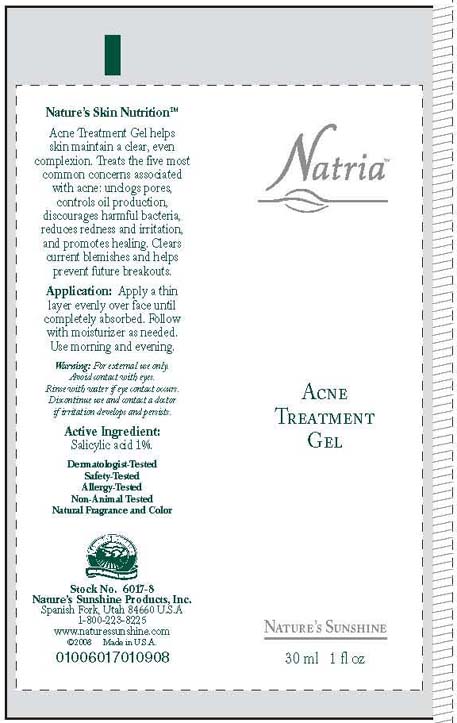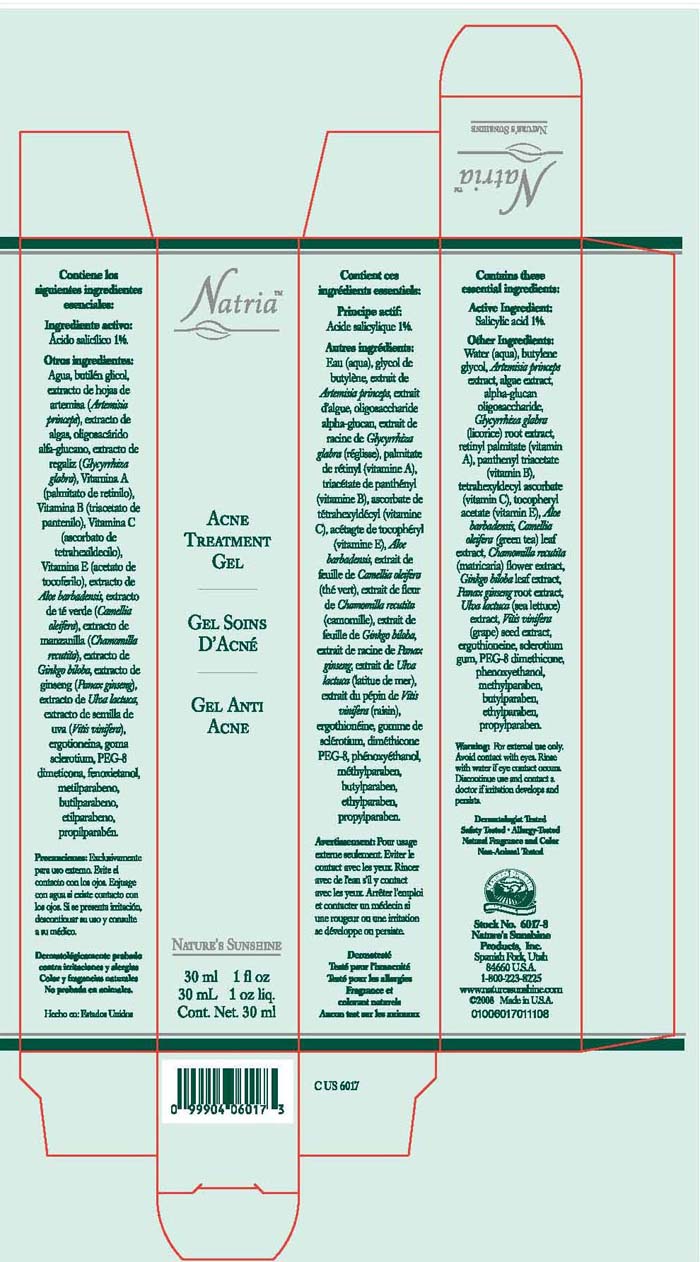 DRUG LABEL: Natria
NDC: 44717-535 | Form: CREAM
Manufacturer: Wasatch Product Development, Inc. 
Category: otc | Type: HUMAN OTC DRUG LABEL
Date: 20100630

ACTIVE INGREDIENTS: SALICYLIC ACID 30 mL/100 mL

Acne Treatment Gel

Active Ingredients

Salicylic Acid 1%

WARNINGS

Warning: For external use only. Avoid contact with eyes. Rinse with water if eye contact occurs. Discontinue use and contact a doctor if irritation develops and persists.

INDICATIONS AND USAGE

Application: Apply a thin layer evenly over face until completely absorbed. Follow with moisturizer as needed. Use morning and evening.

INACTIVE INGREDIENT

Inactive Ingredients: Water (Aqua), Butylene Glycol, Antemisia Princeps extract, algae extract, alpha-glucan oligosaccharide, Glycyrrhiza glabra (licorice) root extract, Retinyl Palmitate (Vitamine A), Panthenyl Triacetate (Vitamin B), Tetrahexyldecyl Ascorbate (Vitamin C), Tocopheryl Acetate (Vitamin E), Aloe Barbadensis, Camellia Oleifera (Green tea) leaf extract, Chamomilla recutita (matricaria) flower extract, Ginkgo biloba leaf extract, panax ginseng root extract, ulva lactuca (sea lettuce) extract, Vitis vinifera (grape) seed extract, ergothioneine, sclerotium gum, PEG-8 dimethicone, Phenoxyethanol, Methylparaben, Butylparaben, Ethylparaben, Propylparaben.

PACKAGE LABEL

Natria

Acne Treatment Gel

30 ml/ 1 fl. oz.